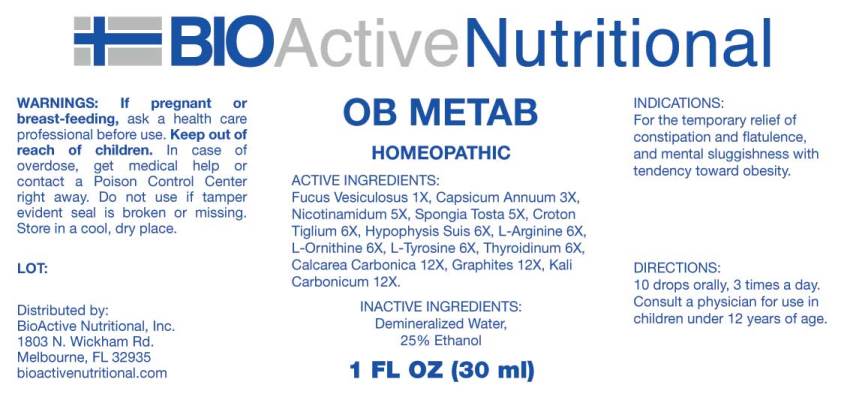 DRUG LABEL: OB Metab
NDC: 43857-0460 | Form: LIQUID
Manufacturer: BioActive Nutritional, Inc.
Category: homeopathic | Type: HUMAN OTC DRUG LABEL
Date: 20170908

ACTIVE INGREDIENTS: FUCUS VESICULOSUS 1 [hp_X]/1 mL; CAPSICUM 3 [hp_X]/1 mL; NIACINAMIDE 5 [hp_X]/1 mL; SPONGIA OFFICINALIS SKELETON, ROASTED 5 [hp_X]/1 mL; CROTON TIGLIUM SEED 6 [hp_X]/1 mL; ARGININE 6 [hp_X]/1 mL; ORNITHINE 6 [hp_X]/1 mL; TYROSINE 6 [hp_X]/1 mL; SUS SCROFA PITUITARY GLAND 6 [hp_X]/1 mL; SUS SCROFA THYROID 6 [hp_X]/1 mL; OYSTER SHELL CALCIUM CARBONATE, CRUDE 12 [hp_X]/1 mL; GRAPHITE 12 [hp_X]/1 mL; POTASSIUM CARBONATE 12 [hp_X]/1 mL
INACTIVE INGREDIENTS: WATER; ALCOHOL

Drug Facts:

ACTIVE INGREDIENTS:

Fucus Vesiculosus 1X, Capsicum Annuum 3X, Nicotinamidum 5X, Spongia Tosta 5X, Croton Tiglium 6X, Hypophysis Suis 6X, L-Arginine 6X, L-Ornithine 6X, L-Tyrosine 6X, Thyroidinum (Suis) 6X, Calcarea Carbonica 12X, Graphites 12X, Kali Carbonicum 12X.

INDICATIONS:

For the temporary relief of constipation and flatulence, and mental sluggishness with tendency toward obesity.

WARNINGS:

If pregnant or breast-feeding, ask a health care professional before use.

Keep out of reach of children. In case of overdose, get medical help or contact a Poison Control Center right away.

Do not use if tamper evident seal is broken or missing.

Store in cool, dry place.

Keep out of reach of children. In case of overdose, get medical help or contact a Poison Control Center right away.

DIRECTIONS:

10 drops orally, 3 times a day. Consult a physician for use in children under 12 years of age.

INDICATIONS:

For the temporary relief of constipation and flatulence, and mental sluggishness with tendency toward obesity.

INACTIVE INGREDIENTS:

Demineralized Water, 25% Ethanol

QUESTIONS:

Distributed by:

BioActive Nutritional, Inc.

1803 N. Wickham Rd.

Melbourne, FL 32935

bioactivenutritional.com

PACKAGE DISPLAY LABEL:

BIOActive Nutritional

OB Metab

HOMEOPATHIC

1 FL OZ (30 ml)